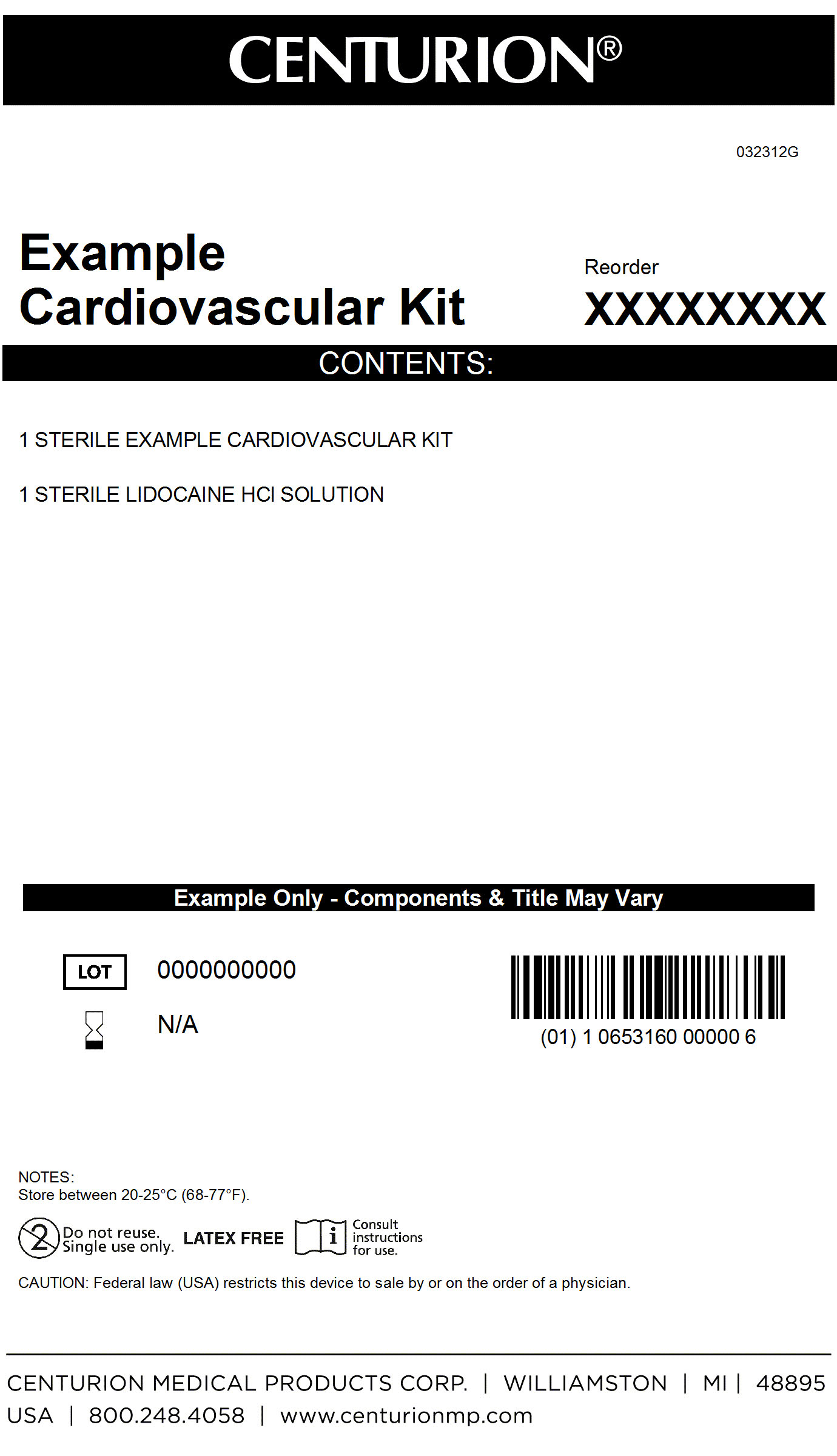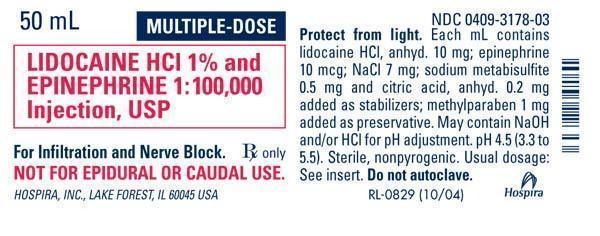 DRUG LABEL: Cardiovascular Procedure Kit
NDC: 24840-1112 | Form: KIT | Route: INFILTRATION
Manufacturer: Centurion Medical Products
Category: other | Type: MEDICAL DEVICE
Date: 20120924

ACTIVE INGREDIENTS: LIDOCAINE HYDROCHLORIDE ANHYDROUS 10 mg/1 mL; EPINEPHRINE 10 ug/1 mL
INACTIVE INGREDIENTS: SODIUM CHLORIDE 7 mg/1 mL; SODIUM METABISULFITE 0.5 mg/1 mL; ANHYDROUS CITRIC ACID 0.2 mg/1 mL; SODIUM HYDROXIDE; HYDROCHLORIC ACID; METHYLPARABEN 1 mg/1 mL; WATER

Cardiovascular Procedure Kit

DESCRIPTION

Lidocaine Hydrochloride and Epinephrine Injection, USP is a sterile, nonpyrogenic solution of lidocaine hydrochloride and epinephrine in water for injection for parenteral administration. Sodium metabisulfate 0.5 mg/ml and citric acid, anhydrous 0.2 mg/ml added as stabilizers. May contain sodium hydroxide and/or hydrochloric acid to adjust pH; pH is 4.5 (3.3 to 5.5). Multiple dose vials contain methylbaraben 1 mg/ml added as preservative. Lidocaine is a local anesthetic of the amide type.

PACKAGE LABEL

MM